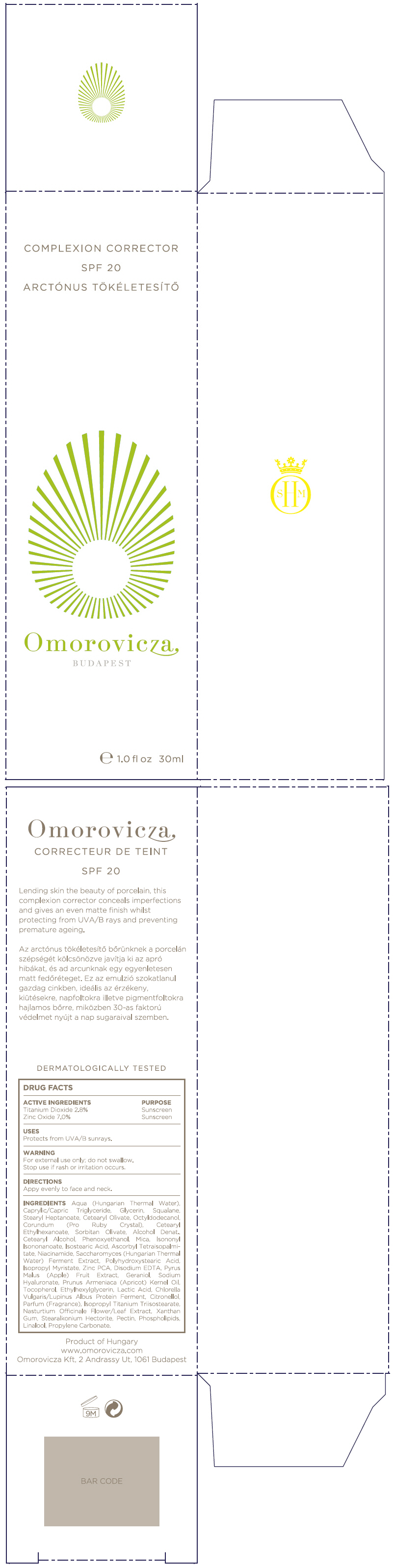 DRUG LABEL: Complexion Corrector SPF20
NDC: 41442-149 | Form: CREAM
Manufacturer: Omorovicza Kozmetikai Kft.
Category: otc | Type: HUMAN OTC DRUG LABEL
Date: 20130125

ACTIVE INGREDIENTS: Titanium Dioxide 28 mg/1 mL; Zinc Oxide 70 mg/1 mL
INACTIVE INGREDIENTS: Caprylic/Capric Mono/Diglycerides; Glycerin; Squalane; Stearyl Heptanoate; Cetearyl Olivate; Octyldodecanol; Cetearyl Ethylhexanoate; Aluminum Oxide; Sorbitan Olivate; Cetostearyl Alcohol; Phenoxyethanol; Mica; Ascorbyl Tetraisopalmitate; Isononyl Isononanoate; Edetate Disodium; Niacinamide; Apple; Isopropyl Myristate; Zinc Pidolate; Hyaluronate Sodium; Geraniol; Ethylhexylglycerin; Apricot Kernel Oil; Tocopherol; Lactic Acid; Glyceryl Isostearate; .Beta.-Citronellol, (+/-)-; Isopropyl Titanium Triisostearate; Xanthan Gum; Pectin; Linalool, (+)-; Nasturtium Officinale Flowering Top; Propylene Carbonate

Complexion Corrector SPF20

DRUG FACTS

ACTIVE INGREDIENT

ACTIVE INGREDIENTS | PURPOSE
Titanium Dioxide 2.8% | Sunscreen
Zinc Oxide 7% | Sunscreen

USES

Protects from UVA/B sunrays.

WARNING

For external use only; do not swallow.

Stop use if rash or irritation occurs.

DIRECTIONS

Appy evenly to face and neck.

INGREDIENTS

Aqua (Hungarian Thermal Water), Caprylic/Capric Triglyceride, Glycerin, Squalane, Stearyl Heptanoate, Cetearyl Olivate, Octyldodecanol, Corundum (Pro Ruby Crystal), Cetearyl Ethylhexanoate, Sorbitan Olivate, Alcohol Denat., Cetearyl Alcohol, Phenoxyethanol, Mica, Isononyl Isononanoate, Isostearic Acid, Ascorbyl Tetraisopalmitate, Niacinamide, Saccharomyces (Hungarian Thermal Water) Ferment Extract, Polyhydroxystearic Acid, Isopropyl Myristate, Zinc PCA, Disodium EDTA, Pyrus Malus (Apple) Fruit Extract, Geraniol, Sodium Hyaluronate, Prunus Armeniaca (Apricot) Kernel Oil, Tocopherol, Ethylhexylglycerin, Lactic Acid, Chlorella Vulgaris/Lupinus Albus Protein Ferment, Citronellol, Parfum (Fragrance), Isopropyl Titanium Triisostearate, Nasturtium Officinale Flower/Leaf Extract, Xanthan Gum, Stearalkonium Hectorite, Pectin, Phospholipids, Linalool, Propylene Carbonate.

Product of Hungary
www.omorovicza.com
Omorovicza Kft, 2 Andrassy Ut, 1061 Budapest

PRINCIPAL DISPLAY PANEL - 30 ml Pump Bottle Carton

COMPLEXION CORRECTOR

SPF 20

Omorovicza

BUDAPEST

e 1.0 fl oz 30ml